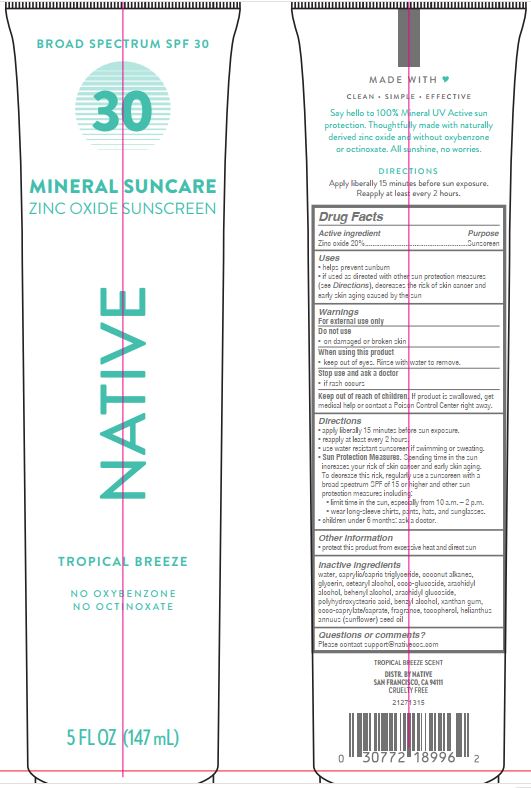 DRUG LABEL: Native Mineral Sunscreen Broad Spectrum SPF 30 Tropical Breeze
NDC: 84126-605 | Form: LOTION
Manufacturer: The Procter & Gamble Manufacturing Company
Category: otc | Type: HUMAN OTC DRUG LABEL
Date: 20251231

ACTIVE INGREDIENTS: ZINC OXIDE 20 g/100 mL
INACTIVE INGREDIENTS: COCONUT ALKANES; COCO GLUCOSIDE; COCO-CAPRYLATE/CAPRATE; WATER; GLYCERIN; TOCOPHEROL; DOCOSANOL; CETOSTEARYL ALCOHOL; POLYHYDROXYSTEARIC ACID (2300 MW); MEDIUM-CHAIN TRIGLYCERIDES; ARACHIDYL ALCOHOL; ARACHIDYL GLUCOSIDE; SUNFLOWER OIL; BENZYL ALCOHOL; XANTHAN GUM

Native Mineral Sunscreen Broad Spectrum SPF 30 Tropical Breeze

Drug Facts

ACTIVE INGREDIENT

ZINC OXIDE 20%

PURPOSE

Sunscreen

Uses

- helps prevent sunburn
- if used as directed with other sun protection measures (see Directions), decreases the risk of skin cancer and early skin aging caused by the sun

Warnings

For external use only

Do not use

- on damaged or broken skin

When using this product

- keep out of eyes. Rinse with water to remove.

Stop use and ask a doctor if

- rash occurs

Keep out of reach of children.If product is swallowed, get medical help or contact a Poison Control Center right away.

Directions

- apply liberally 15 minutes before sun exposure
- reapply at least every 2 hours
- use water resistant sunscreen if swimming or sweating
- Sun Protection Measures.Spending time in the sun increases your risk of skin cancer and early skin aging. To decrease this risk, regularly use a sunscreen with a Broad Spectrum SPF value of 15 or higher and other sun protection measures including:
  - limit time in sun, especially from 10 a.m. – 2 p.m.
  - wear long-sleeved shirts, pants, hats, and sunglasses
- children under 6 months: ask a doctor

Other information

- protect this product from excessive heat and direct sun

Inactive ingredients

water, caprylic/capric triglyceride, coconut alkanes, glycerin, cetearyl alcohol, coco-glucoside, arachidyl alcohol, behenyl alcohol, arachidyl glucoside, polyhydroxystearic acid, benzyl alcohol, xanthan gum, coco-caprylate/caprate, fragrance, tocopherol, helianthus annuus (sunflower) seed oil

Distr. by Native San Francisco, CA 94111

Questions or comments?

Please contact support@nativecos.com

PRINCIPAL DISPLAY PANEL - 147 mL Tube

BROAD SPECTRUM SPF 30

MINERAL SUNCARE

ZINC OXIDE SUNSCREEN

NATIVE

TROPICAL BREEZE

NO OXYBENZONE

NO OCTINOXATE

5 FL OZ (147 mL)